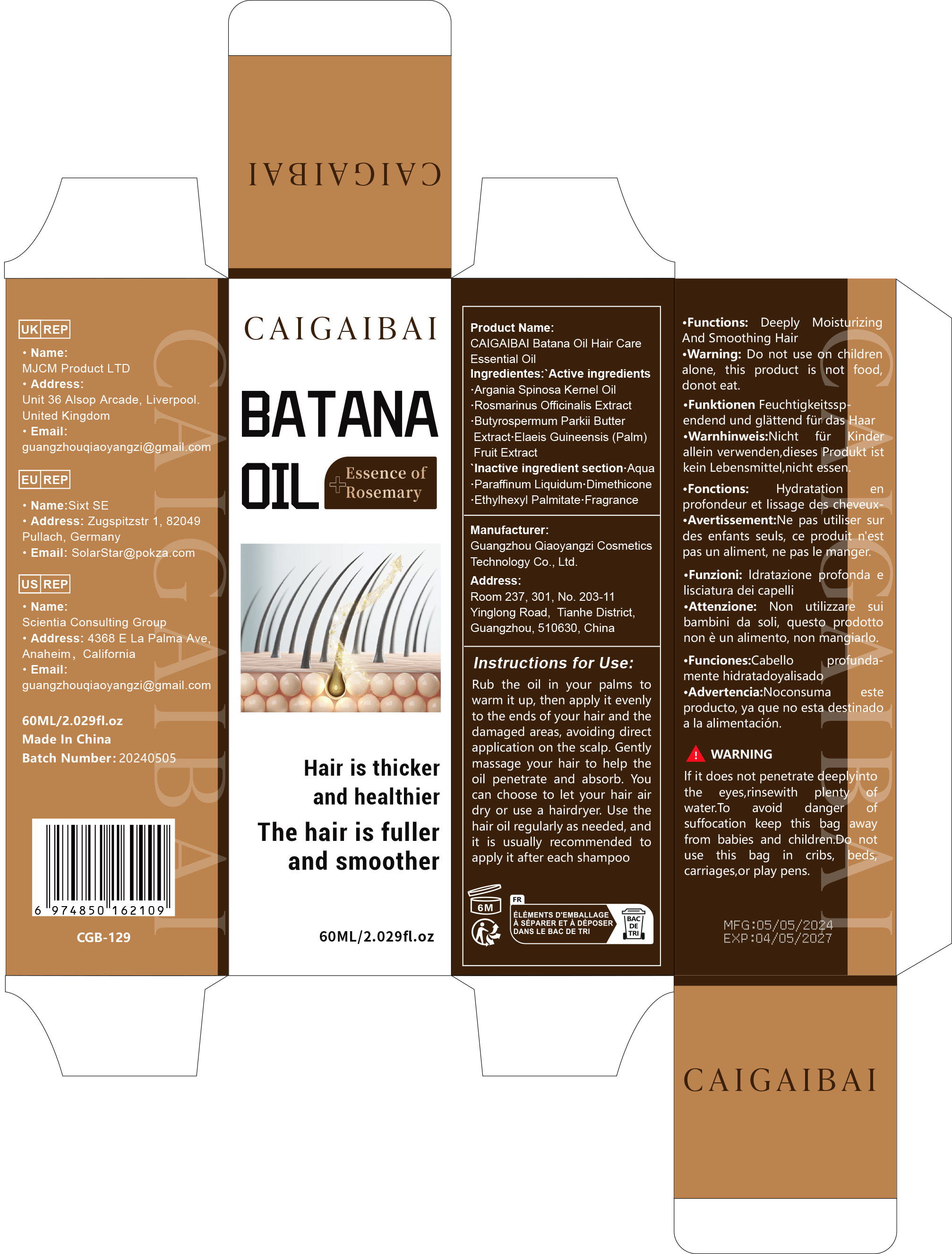 DRUG LABEL: Batana Oil Hair Care Essential Oil
NDC: 84751-129 | Form: OIL
Manufacturer: Guangzhou Qiaoyangzi Cosmetics Technology Co Ltd
Category: otc | Type: HUMAN OTC DRUG LABEL
Date: 20241030

ACTIVE INGREDIENTS: BUTYROSPERMUM PARKII (SHEA) BUTTER EXTRACT 0.35 mg/60 mL; ARGANIA SPINOSA KERNEL OIL 2 mg/60 mL; ROSMARINUS OFFICINALIS (ROSEMARY) EXTRACT 1 mg/60 mL; ELAEIS GUINEENSIS FRUIT 0.2 mg/60 mL
INACTIVE INGREDIENTS: AQUA 57.45 mg/60 mL

Active ingredients

Argania Spinosa Kernel Oil 2.00%
Rosmarinus Officinalis Extract 1.00%
Butyrospermum Parkii Butter Extract 0.35%
Elaeis Guineensis (Palm) Fruit Extract 0.20%

INACTIVE INGREDIENT SECTION

Aqua 57.45%
Paraffinum Liquidum 35.00%
Dimethicone 1.30%
Ethylhexyl Palmitate 2.50%
Fragrance 0.20%

Purpose

Repair damaged hair.

Uses

Rub the oil in your palms to warm it up, then apply it evenly to the ends of your hair and the damaged areas, avoiding direct application on the scalp. Gently massage your hair to help the oil penetrate and absorb. You can choose to let your hair air dry or use a hairdryer. Use the hair oil regularly as needed, and it is usually recommended to apply it after each shampoo

Warnings

Do not enter the eyes when using. Rinse with plenty ofwater and keep out of reach of children. Not edible

Stop use

Discontinue Use Section

Allergic Reactions
If you experience an allergic reaction, such as itching, redness, or swelling, discontinue use immediately.

Skin Irritation
If you feel severe irritation or burning sensation during use, stop using the product.

Eye Contact
Avoid contact with eyes. If contact occurs, rinse immediately with water and consult a doctor if discomfort persists.

Discomfort After Use
If you experience any other discomfort after using the product (such as headaches or dizziness), discontinue use.

Contraindications
Consult a doctor before use if you are pregnant, breastfeeding, or have specific health conditions (such as skin diseases or heart problems).

Do not use

Contraindications Section

Known Allergies
Do not use if you are known to be allergic to any ingredients in this product.

Open Wounds
Do not use on open wounds or inflamed skin.

Severe Skin Conditions
Do not use if you have a history of severe skin conditions (such as eczema or psoriasis).

Pregnancy or Breastfeeding
Do not use if you are pregnant or breastfeeding.

Children
Do not use in children under 12 years of age.

Keep out of reach of children!

To avoid danger of suffocation, keep this bag away from babies and children. Do not use this bag in cribs, beds, carriages, or play pens. This bag is not a toy.

Precautions for Use

lf it does not penetrate deeplyinto the eyes, rinse
with plenty of water.Do not use on children alone, this product is not food,
do not eat.

Instructions for Use

Rub the oil in your palms to warm it up, then apply it evenly to the ends of your hair and the damaged areas, avoiding direct application on the scalp. Gently massage your hair to help the oil penetrate and absorb. You can choose to let your hair air dry or use a hairdryer. Use the hair oil regularly as needed, and it is usually recommended to apply it after each shampoo

DOSAGE & ADMINISTRATION SECTION

Dosage and Administration Section

Recommended Dose
Apply an appropriate amount (e.g., 3-5 drops) evenly to the targeted area.

Frequency of Use
Use 1-2 times daily, preferably once in the morning and once in the evening.

Application Method
Gently massage until fully absorbed, ensuring even distribution of the product.

Storage Conditions
Store in a cool, dry place away from direct sunlight.

Overuse
If excess product is used, rinse with water and consult a doctor.